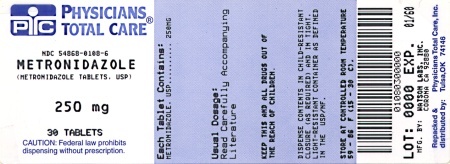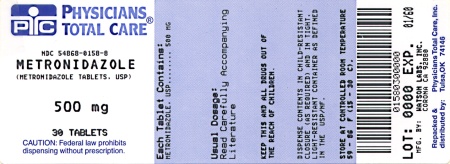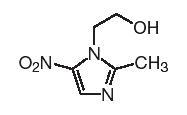 DRUG LABEL: Metronidazole
NDC: 54868-0108 | Form: TABLET
Manufacturer: Physicians Total Care, Inc.
Category: prescription | Type: HUMAN PRESCRIPTION DRUG LABEL
Date: 20130722

ACTIVE INGREDIENTS: METRONIDAZOLE 250 mg/1 1
INACTIVE INGREDIENTS: SILICON DIOXIDE; CROSPOVIDONE; CELLULOSE, MICROCRYSTALLINE

WARNING

To reduce the development of drug-resistant bacteria and maintain the effectiveness of metronidazole tablets and other antibacterial drugs, metronidazole tablets should be used only to treat or prevent infections that are proven or strongly suspected to be caused by bacteria.

Metronidazole has been shown to be carcinogenic in mice and rats. (See PRECAUTIONS.) Unnecessary use of the drug should be avoided. Its use should be reserved for the conditions described in the INDICATIONS AND USAGE section below.

DESCRIPTION

Metronidazole is an oral synthetic antiprotozoal and antibacterial agent, 1-(β-hydroxyethyl)-2-methyl-5-nitroimidazole. The structural formula is represented below:

 | C6H9N3O3 | M.W. 171.15

Each tablet, for oral administration, contains 250 mg or 500 mg of metronidazole. In addition, each tablet contains the following inactive ingredients: colloidal silicon dioxide, crospovidone, hydrogenated vegetable oil and microcrystalline cellulose.

CLINICAL PHARMACOLOGY

Disposition of metronidazole in the body is similar for both oral and intravenous dosage forms, with an average elimination half-life in healthy humans of eight hours.

The major route of elimination of metronidazole and its metabolites is via the urine (60 to 80% of the dose), with fecal excretion accounting for 6 to 15% of the dose. The metabolites that appear in the urine result primarily from side-chain oxidation [1-(β-hydroxyethyl)-2-hydroxymethyl-5- nitroimidazole and 2-methyl-5-nitroimidazole-1-yl-acetic acid] and glucuronide conjugation, with unchanged metronidazole accounting for approximately 20% of the total. Renal clearance of metronidazole is approximately 10 mL/min/1.73 m^2.

Metronidazole is the major component appearing in the plasma, with lesser quantities of the 2-hydroxymethyl metabolite also being present. Less than 20% of the circulating metronidazole is bound to plasma proteins. Both the parent compound and the metabolite possess in vitro bactericidal activity against most strains of anaerobic bacteria and in vitro trichomonacidal activity.

Metronidazole appears in cerebrospinal fluid, saliva, and human milk in concentrations similar to those found in plasma. Bactericidal concentrations of metronidazole have also been detected in pus from hepatic abscesses.

Following oral administration, metronidazole is well absorbed, with peak plasma concentrations occurring between one and two hours after administration. Plasma concentrations of metronidazole are proportional to the administered dose. Oral administration of 250 mg, 500 mg, or 2,000 mg produced peak plasma concentrations of 6 mcg/mL, 12 mcg/mL, and 40 mcg/mL, respectively. Studies reveal no significant bioavailability differences between males and females; however, because of weight differences, the resulting plasma levels in males are generally lower.

Decreased renal function does not alter the single-dose pharmacokinetics of metronidazole. However, plasma clearance of metronidazole is decreased in patients with decreased liver function.

Microbiology

Trichomonas vaginalis, Entamoeba histolytica

Metronidazole possesses direct trichomonacidal and amebacidal activity against T. vaginalis and E. histolytica. The in vitro minimal inhibitory concentration (MIC) for most strains of these organisms is 1 mcg/mL or less.

Anaerobic Bacteria

Metronidazole is active in vitro against most obligate anaerobes but does not appear to possess any clinically relevant activity against facultative anaerobes or obligate aerobes. Against susceptible organisms, metronidazole is generally bactericidal at concentrations equal to or slightly higher than the minimal inhibitory concentrations. Metronidazole has been shown to have in vitro and clinical activity against the following organisms:

Anaerobic gram-negative bacilli, including:

Bacteroides species including the Bacteroides fragilis group (B.fragilis, B.ovatus, B.distasonis, B.thetaiotaomicron, B.vulgatus)

Fusobacterium species

Anaerobic gram-positive bacilli, including:

Clostridium species and susceptible strains of Eubacterium

Anaerobic gram-positive cocci, including:

Peptococcus niger

Peptostreptococcus species

Susceptibility Tests

Bacteriologic studies should be performed to determine the causative organisms and their susceptibility to metronidazole; however, the rapid, routine susceptibility testing of individual isolates of anaerobic bacteria is not always practical, and therapy may be started while awaiting these results.

Quantitative methods give the most precise estimates of susceptibility testing. Each time the tests is performed, one or more of the following strains should be included: Clostridium perfringens ATCC 13124, Bacteroides fragilis ATCC 25285, and Bacteroides thetaiotaomicron ATCC 29741. The mode metronidazole MICs for those three strains are reported to be 0.25, 0.25, and 0.5 mcg/mL, respectively.

A clinical laboratory is considered under acceptable control is the results of the control strains are within one doubling dilution of the mode MICs reported for metronidazole.

A bacterial isolate may be considered susceptible if the MIC value for metronidazole is not more than 16 mcg/mL. An organism is considered resistant if the MIC is greater than 16 mcg/mL. A report of "resistant" from the laboratory indicates that the infecting organism is not likely to respond to therapy.

INDICATIONS AND USAGE

Symptomatic Trichomoniasis

Metronidazole is indicated for the treatment of symptomatic trichomoniasis in females and males when the presence of the trichomonad has been confirmed by appropriate laboratory procedures (wet smears and/or cultures).

Asymptomatic Trichomoniasis

Metronidazole is indicated in the treatment of asymptomatic females when the organism is associated with endocervicitis, cervicitis, or cervical erosion. Since there is evidence that presence of the trichomonad can interfere with accurate assessment of abnormal cytological smears, additional smears should be performed after eradication of the parasite.

Treatment of Asymptomatic Consorts

T. vaginalis infection is a venereal disease. Therefore, asymptomatic sexual partners of treated patients should be treated simultaneously if the organism has been found to be present, in order to prevent reinfection of the partner. The decision as to whether to treat an asymptomatic male partner who has a negative culture or one for whom no culture has been attempted is an individual one. In making this decision, it should be noted that there is evidence that a woman may become reinfected if her consort is not treated. Also, since there can be considerable difficulty in isolating the organism from the asymptomatic male carrier, negative smears and cultures cannot be relied upon in this regard. In any event, the consort should be treated with metronidazole in cases of reinfection.

Amebiasis

Metronidazole is indicated in the treatment of acute intestinal amebiasis (amebic dysentery) and amebic liver abscess.

In amebic liver abscess, metronidazole therapy does not obviate the need for aspiration or drainage of pus.

Anaerobic Bacterial Infections

Metronidazole is indicated in the treatment of serious infections caused by susceptible anaerobic bacteria. Indicated surgical procedures should be performed in conjunction with metronidazole therapy. In a mixed aerobic and anaerobic infection, antimicrobials appropriate for the treatment of the aerobic infection should be used in addition to metronidazole.

In the treatment of most serious anaerobic infections, the intravenous form of metronidazole is usually administered initially. This may be followed by oral therapy with metronidazole at the discretion of the physician.

INTRA-ABDOMINAL INFECTIONS, including peritonitis, intra-abdominal abscess, and liver abscess, caused by Bacteroides species including the B. fragilis group (B. fragilis, B. distasonis, B. ovatus, B. thetaiotaomicron, B. vulgatus), Clostridium species, Eubacterium species, Peptococcus niger, and Peptostreptococcus species.

SKIN AND SKIN STRUCTURE INFECTIONS caused by Bacteroides species including the B . fragilis group, Clostridium species, Peptococcus niger, Peptostreptococcus species, and Fusobacterium species.

GYNECOLOGIC INFECTIONS, including endometritis, endomyometritis, tubo-ovarian abscess, and post-surgical vaginal cuff infection, caused by Bacteroides species including the B. fragilis group, Clostridium species, Peptococcus niger, and Peptostreptococcus species.

BACTERIAL SEPTICEMIA caused by Bacteroides species including the B. fragilis group, and Clostridium species.

BONE AND JOINT INFECTIONS, as adjunctive therapy, caused by Bacteroides species including the B. fragilis group.

CENTRAL N E RVOUS SYSTEM (CNS) INFECTIONS, including meningitis and brain abscess, caused by Bacteroides species including the B. fragilis group.

LOWER RESPIRATO RY TRACT INFECTIONS, including pneumonia, empyema, and lung abscess, caused by Bacteroides species including the B. fragilis group.

ENDOCARDITIS caused by Bacteroides species including the B. fragilis group.

To reduce the development of drug-resistant bacteria and maintain the effectiveness of metronidazole tablets and other antibacterial drugs, metronidazole tablets should be used only to treat or prevent infections that are proven or strongly suspected to be caused by susceptible bacteria. When culture and susceptibility information are available, they should be considered in selecting or modifying antibacterial therapy. In the absence of such data, local epidemiology and susceptibility patterns may contribute to the empiric selection of therapy.

CONTRAINDICATIONS

Metronidazole is contraindicated in patients with a prior history of hypersensitivity to metronidazole or other nitroimidazole derivatives.

In patients with trichomoniasis, metronidazole is contraindicated during the first trimester of pregnancy. (See PRECAUTIONS.)

WARNINGS

Convulsive Seizures and Peripheral Neuropathy

Convulsive seizures and peripheral neuropathy, the latter characterized mainly by numbness or paresthesia of an extremity, have been reported in patients treated with metronidazole. The appearance of abnormal neurologic signs demands the prompt discontinuation of metronidazole therapy. Metronidazole should be administered with caution to patients with central nervous system diseases.

PRECAUTIONS

General

Patients with severe hepatic disease metabolize metronidazole slowly, with resultant accumulation of metronidazole and its metabolites in the plasma. Accordingly, for such patients, doses below those usually recommended should be administered cautiously.

Known or previously unrecognized candidiasis may present more prominent symptoms during therapy with metronidazole and requires treatment with a candidacidal agent.

Prescribing metronidazole tablets in the absence of a proven or strongly suspected bacterial infection or a prophylactic indication is unlikely to provide benefit to the patient and increases the risk of the development of drug-resistant bacteria.

Information for Patients

Alcoholic beverages should be avoided while taking metronidazole and for at least one day afterward. (See Drug Interactions.)

Patients should be counseled that antibacterial drugs including metronidazole tablets should only be used to treat bacterial infections. They do not treat viral infections (e.g., the common cold). When metronidazole tablets are prescribed to treat a bacterial infection, patients should be told that although it is common to feel better early in the course of therapy, the medication should be taken exactly as directed. Skipping doses or not completing the full course of therapy may (1) decrease the effectiveness of the immediate treatment and (2) increase the likelihood that bacteria will develop resistance and will not be treatable by metronidazole tablets or other antibacterial drugs in the future.

Laboratory Tests

Metronidazole is a nitroimidazole and should be used with caution in patients with evidence of or history of blood dyscrasia. A mild leukopenia has been observed during its administration; however, no persistent hematologic abnormalities attributable to metronidazole have been observed in clinical studies. Total and differential leukocyte counts are recommended before and after therapy for trichomoniasis and amebiasis, especially if a second course of therapy is necessary, and before and after therapy for anaerobic infections.

Drug Interactions

Metronidazole has been reported to potentiate the anticoagulant effect of warfarin and other oral coumarin anticoagulants, resulting in a prolongation of prothrombin time. This possible drug interaction should be considered when metronidazole is prescribed for patients on this type of anticoagulant therapy.

The simultaneous administration of drugs that induce microsomal liver enzymes, such as phenytoin or phenobarbital, may accelerate the elimination of metronidazole, resulting in reduced plasma levels; impaired clearance of phenytoin has also been reported.

The simultaneous administration of drugs that decrease microsomal liver enzyme activity, such as cimetidine, may prolong the half-life and decrease plasma clearance of metronidazole. In patients stabilized on relatively high doses of lithium, short-term metronidazole therapy has been associated with elevation of serum lithium and, in a few cases, signs of lithium toxicity. Serum lithium and serum creatinine levels should be obtained several days after beginning metronidazole to detect any increase that may precede clinical symptoms of lithium intoxication.

Alcoholic beverages should not be consumed during metronidazole therapy and for at least one day afterward because abdominal cramps, nausea, vomiting, headaches, and flushing may occur.

Psychotic reactions have been reported in alcoholic patients who are using metronidazole and disulfiram concurrently. Metronidazole should not be given to patients who have taken disulfiram within the last two weeks.

Drug/Laboratory Test Interactions

Metronidazole may interfere with certain types of determinations of serum chemistry values, such as aspartate aminotransferase (AST, SGOT), alanine aminotransferase (ALT, SGPT), lactate dehydrogenase (LDH), triglycerides, and hexokinase glucose. Values of zero may be observed. All of the assays in which interference has been reported involve enzymatic coupling of the assay to oxidation-reduction of nicotinamide adenine dinucleotide (NAD+ ↔ NADH). Interference is due to the similarity in absorbance peaks of NADH (340 nm) and metronidazole (322 nm) at pH 7.

Carcinogenesis, Mutagenesis, Impairment of Fertility

Metronidazole has shown evidence of carcinogenic activity in a number of studies involving chronic, oral administration in mice and rats.

Prominent among the effects in the mouse was the promotion of pulmonary tumorigenesis. This has been observed in all six reported studies in that species, including one study in which the animals were dosed on an intermittent schedule (administration during every fourth week only). At very high dose levels (approx. 500 mg/kg/day which is approximately 33 times the most frequently recommended human dose for a 50 kg adult based on mg/kg body weight) there was a statistically significant increase in the incidence of malignant liver tumors in males. Also, the published results of one of the mouse studies indicate an increase in the incidence of malignant lymphomas as well as pulmonary neoplasms associated with lifetime feeding of the drug. All these effects are statistically significant.

Several long-term, oral-dosing studies in the rat have been completed. There were statistically significant increases in the incidence of various neoplasms, particularly in mammary and hepatic tumors, among female rats administered metronidazole over those noted in the concurrent female control groups.

Two lifetime tumorigenicity studies in hamsters have been performed and reported to be negative.

Although metronidazole has shown mutagenic activity in a number of in vitro assay systems, studies in mammals (in vivo) have failed to demonstrate a potential for genetic damage.

Fertility studies have been performed in mice at doses up to six times the maximum recommended human dose based on mg/m^2 and have revealed no evidence of impaired fertility.

Pregnancy

Teratogenic Effects-Pregnancy Category B

Metronidazole crosses the placental barrier and enters the fetal circulation rapidly. Reproduction studies have been performed in rats at doses up to five times the human dose and have revealed no evidence of impaired fertility or harm to the fetus due to metronidazole. No fetotoxicity was observed when metronidazole was administered orally to pregnant mice at 20 mg/kg/day, approximately one and a half times the most frequently recommended human dose (750 mg/day) based on mg/kg body weight; however, in a single small study where the drug was administered intraperitoneally, some intrauterine deaths were observed. The relationship of these findings to the drug is unknown. There are, however, no adequate and well-controlled studies in pregnant women. Because animal reproduction studies are not always predictive of human response, and because metronidazole is a carcinogen in rodents, this drug should be used during pregnancy only if clearly needed.

Use of metronidazole for trichomoniasis during pregnancy should be restricted to those in whom alternative treatment has been inadequate. Use of metronidazole for trichomoniasis in pregnancy should be carefully evaluated because metronidazole crosses the placental barrier and its effects on the human fetal organogenesis are not known (see above).

Nursing Mothers

Because of the potential for tumorigenicity, shown for metronidazole in mouse and rat studies, a decision should be made whether to discontinue nursing or to discontinue the drug, taking into account the importance of the drug to the mother. Metronidazole is secreted in human milk in concentrations similar to those found in plasma.

Geriatric Use

Decreased renal function does not alter the single-dose pharmacokinetics of metronidazole. However, plasma clearance of metronidazole is decreased in patients with decreased liver function. Therefore, in elderly patients, monitoring of serum levels may be necessary to adjust the metronidazole dosage accordingly.

Pediatric Use

Safety and effectiveness in pediatric patients have not been established, except for the treatment of amebiasis.

ADVERSE REACTIONS

Two serious adverse reactions reported in patients treated with metronidazole have been convulsive seizures and peripheral neuropathy, the latter characterized mainly by numbness or paresthesia of an extremity. Since persistent peripheral neuropathy has been reported in some patients receiving prolonged administration of metronidazole, patients should be specifically warned about these reactions and should be told to stop the drug and report immediately to their physicians if any neurologic symptoms occur.

The most common adverse reactions reported have been referable to the gastrointestinal tract, particularly nausea reported by about 12% of patients, sometimes accompanied by headache, anorexia, and occasionally vomiting; diarrhea; epigastric distress; and abdominal cramping. Constipation has also been reported.

The following reactions have also been reported during treatment with metronidazole:

Mouth

A sharp, unpleasant metallic taste is not unusual. Furry tongue, glossitis, and stomatitis have occurred; these may be associated with a sudden overgrowth of Candida which may occur during therapy.

Hematopoietic

Reversible neutropenia (leukopenia); rarely, reversible thrombocytopenia.

Cardiovascular

Flattening of the T-wave may be seen in electrocardiographic tracings.

Central Nervous System

Convulsive seizures, peripheral neuropathy, dizziness, vertigo, incoordination, ataxia, confusion, irritability, depression, weakness, and insomnia.

Hypersensitivity

Urticaria, erythematous rash, flushing, nasal congestion, dryness of the mouth (or vagina or vulva), and fever.

Renal

Dysuria, cystitis, polyuria, incontinence, and a sense of pelvic pressure. Instances of darkened urine have been reported by approximately one patient in 100,000. Although the pigment which is probably responsible for this phenomenon has not been positively identified, it is almost certainly a metabolite of metronidazole and seems to have no clinical significance.

Other

Proliferation of Candida in the vagina, dyspareunia, decrease of libido, proctitis, and fleeting joint pains sometimes resembling “serum sickness.” If patients receiving metronidazole drink alcoholic beverages, they may experience abdominal distress, nausea, vomiting, flushing, or headache. A modification of the taste of alcoholic beverages has also been reported. Rare cases of pancreatitis, which generally abated on withdrawal of the drug, have been reported.

Crohn’s disease patients are known to have an increased incidence of gastrointestinal and certain extraintestinal cancers. There have been some reports in the medical literature of breast and colon cancer in Crohn’s disease patients who have been treated with metronidazole at high doses for extended periods of time. A cause and effect relationship has not been established. Crohn’s disease is not an approved indication for metronidazole.

OVERDOSAGE

Single oral doses of metronidazole, up to 15 g, have been reported in suicide attempts and accidental overdoses. Symptoms reported include nausea, vomiting, and ataxia.

Oral metronidazole has been studied as a radiation sensitizer in the treatment of malignant tumors. Neurotoxic effects, including seizures and peripheral neuropathy, have been reported after 5 to 7 days of doses of 6 to 10.4 g every other day.

Treatment

There is no specific antidote for metronidazole overdose; therefore, management of the patient should consist of symptomatic and supportive therapy.

DOSAGE AND ADMINISTRATION

In elderly patients, the pharmacokinetics of metronidazole may be altered, and, therefore, monitoring of serum levels may be necessary to adjust the metronidazole dosage accordingly.

Trichomoniasis

In the Female

One-day treatment— two grams of metronidazole, given either as a single dose or in two divided doses of one gram each given in the same day.

Seven-day course of treatment— 250 mg three times daily for seven consecutive days. There is some indication from controlled comparative studies that cure rates as determined by vaginal smears, signs and symptoms, may be higher after a seven-day course of treatment than after a one-day treatment regimen.

The dosage regimen should be individualized. Single-dose treatment can assure compliance, especially if administered under supervision, in those patients who cannot be relied on to continue the seven-day regimen. A seven-day course of treatment may minimize reinfection by protecting the patient long enough for the sexual contacts to obtain appropriate treatment. Further, some patients may tolerate one treatment regimen better than the other.

Pregnant patients should not be treated during the first trimester. (See CONTRAINDICATIONS.) In pregnant patients in whom alternative treatment has been inadequate, the one-day course of therapy should not be used, as it results in higher serum levels which can reach the fetal circulation (see PRECAUTIONS, Pregnancy).

When repeat courses of the drug are required, it is recommended that an interval of four to six weeks elapse between courses and that the presence of the trichomonad be reconfirmed by appropriate laboratory measures. Total and differential leukocyte counts should be made before and after retreatment.

In the Male

Treatment should beindividualized as for the female.

Amebiasis

Adults

For acute intestinal amebiasis (acute amebic dysentery): 750 mg orally three times daily for 5 to 10 days.

For amebic liver abscess: 500 mg or 750 mg orally three times daily for 5 to 10 days.

Pediatric patients

35 to 50 mg/kg/24 hours, divided into three doses, orally for 10 days.

Anaerobic Bacterial Infections

In the treatment of most serious anaerobic infections, the intravenous form of metronidazole is usually administered initially.

The usual adult oral dosage is 7.5 mg/kg every six hours (approx. 500 mg for a 70-kg adult). A maximum of 4 g should not be exceeded during a 24-hour period.

The usual duration of therapy is 7 to 10 days; however, infections of the bone and joint, lower respiratory tract, and endocardium may require longer treatment.

Patients with severe hepatic disease metabolize metronidazole slowly, with resultant accumulation of metronidazole and its metabolites in the plasma. Accordingly, for such patients, doses below those usually recommended should be administered cautiously. Close monitoring of plasma metronidazole levels^2 and toxicity is recommended.

The dose of metronidazole should not be specifically reduced in anuric patients since accumulated metabolites may be rapidly removed by dialysis.

HOW SUPPLIED

Metronidazole Tablets USP 250 mg are 11/32״, unscored, round, white to off-white tablets imprinted DAN and 5540 supplied in:

NDC 54868-0108-2 | Bottles of 10
NDC 54868-0108-8 | Bottles of 14
NDC 54868-0108-3 | Bottles of 20
NDC 54868-0108-1 | Bottles of 21
NDC 54868-0108-6 | Bottles of 30
NDC 54868-0108-7 | Bottles of 100

Metronidazole Tablets USP 500 mg are 17/32״, scored, round, white to off-white tablets imprinted DAN and 5552 supplied in:

NDC 54868-0158-3 | Bottles of 10
NDC 54868-0158-1 | Bottles of 14
NDC 54868-0158-5 | Bottles of 20
NDC 54868-0158-0 | Bottles of 21
NDC 54868-0158-8 | Bottles of 30
NDC 54868-0158-6 | Bottles of 40
NDC54868-0158-2 | Bottles of 4

Dispense in a well-closed, light-resistant container with child-resistant closure.

Store below 86°F (30°C).

Protect from light.

REFERENCES

1. Proposed standard: PSM-11-Proposed Reference Dilution Procedure for Antimicrobic Susceptibility Testing of Anaerobic Bacteria, National Committee for Clinical Laboratory Standards; and Sutter, et al.: Collaborative Evaluation of a Proposed Reference Dilution Method of Susceptibility Testing of Anaerobic Bacteria, Antimicrob. Agents Chemother. 16:495-502 (Oct.) 1979; and Tally, et al.: In Vitro Activity of Thienamycin, Antimicrob. Agents Chemother. 14:436-438 (Sept.) 1978.
2. Ralph, E.D., and Kirby, W.M.M.: Bioassay of Metronidazole With Either Anaerobic or Aerobic Incubation, J. Infect. Dis.132:587-591 (Nov.) 1975; or Gulaid, et al.: Determination of Metronidazole and Its Major Metabolites in Biological Fluids by High Pressure Liquid Chromatography, Br. J. Clin. Pharmacol. 6:430-432, 1978.

Relabeling and Repackaging by:

Physicians Total Care, Inc.
Tulsa, Oklahoma 74146

PRINCIPAL DISPLAY PANEL

Metronidazole Tablets USP

250 mg

Metronidazole Tablets USP

500 mg